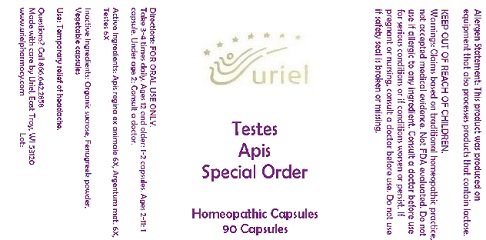 DRUG LABEL: Testes Apis Special Order
NDC: 48951-9196 | Form: CAPSULE
Manufacturer: Uriel Pharmacy Inc.
Category: homeopathic | Type: HUMAN OTC DRUG LABEL
Date: 20180501

ACTIVE INGREDIENTS: ROYAL JELLY 6 [hp_X]/1 1; SILVER 6 [hp_X]/1 1; BOS TAURUS TESTICLE 6 [hp_X]/1 1
INACTIVE INGREDIENTS: SUCROSE; FENUGREEK LEAF; POWDERED CELLULOSE

Testes Apis Special Order

INDICATIONS AND USAGE

Directions: FOR ORAL USE ONLY.

DOSAGE AND ADMINISTRATION

Take 3-4 times daily. Ages 12 and older: 1-2 capsules. Ages 2-11: 1 capsule. Under age 2: Consult a doctor.

ACTIVE INGREDIENT

Active Ingredients: Apis regina ex animale 6X, Argentum met. 6X, Testes 6X

INACTIVE INGREDIENT

Inactive Ingredients: Organic sucrose, Fenugreek powder, Vegetable capsules

PURPOSE

Use: Temporary relief of headache.

KEEP OUT OF REACH OF CHILDREN.

WARNINGS

Allergen Statement: This product was produced on equipment that also processes products that contain lactose.

Warnings: Claims based on traditional homeopathic practice, not accepted medical evidence. Not FDA evaluated. Do not use if allergic to any ingredient. Consult a doctor before use for serious conditions or if conditions worsen or persist. If pregnant or nursing, consult a doctor before use. Do not use if safety seal is broken or missing.

QUESTIONS

Questions? Call 866.642.2858 Made with care by Uriel, East Troy, WI 53120 www.urielpharmacy.com